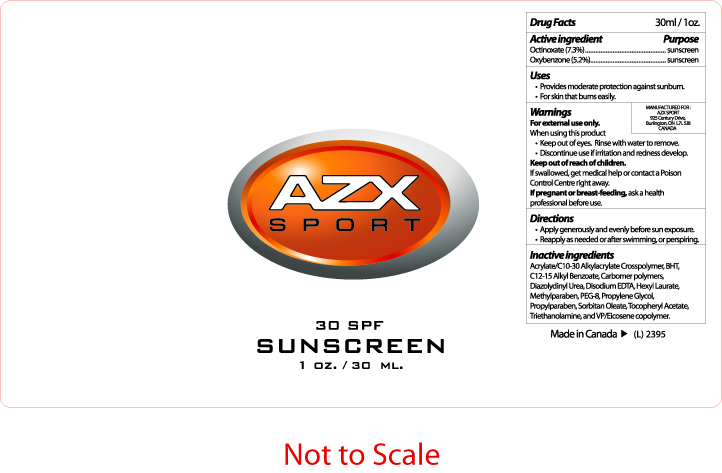 DRUG LABEL: Sunscreen
NDC: 75887-003 | Form: LOTION
Manufacturer: Aztex Enterprises
Category: otc | Type: HUMAN OTC DRUG LABEL
Date: 20110118

ACTIVE INGREDIENTS: OCTINOXATE 22 mL/30 mL; OXYBENZONE 16 mL/30 mL
INACTIVE INGREDIENTS: CARBOMER INTERPOLYMER TYPE A (55000 CPS); BUTYLATED HYDROXYTOLUENE; ALKYL (C12-15) BENZOATE; CARBOMER 1342; UREA; EDETATE DISODIUM; HEXYL LAURATE; METHYLPARABEN; PROPYLPARABEN; POLYETHYLENE GLYCOL 400; SORBITAN MONOOLEATE; .ALPHA.-TOCOPHEROL ACETATE, D-; PROPYLENE GLYCOL; TROLAMINE

ACTIVE INGREDIENT

Drug Facts 30ml/1oz.
Active Ingredient Purpose
Octinoxate (7.3%) sunscreen
Oxybenzone (5.2%) sunscreen

Uses
Provides moderate protection against sunburn
For skin that burns easily

Warnings
For external use only.
When using this produce
Keep out of eyes, rinse with water to remove
Discontinue use of irritation and redness develop
Keep out of reach of children
If swallowed, get medical help or contact a Poison Control Center right away
If pregnant or breastfeeding, ask a health care professional before use

Directions
Apply generously and evenly before sun exposure
Reapply as needed or after swimming or perspiring

Inactive Ingredients
Acrylate/C10-30 Alkylacrylate Crosspolymer
BHT
C12-15 Alkyl Benzoate
Carbomer polymers
Diazolydinyl Urea
Disodium EDTA
Hexyl Laurate
Methylparaben, Propylparaben
PEG-8, Sorbitan Oleate, Tocopheryl Acetate
Propylene Glycol, Triethanolamine, VP/Eicosene copolymer

PACKAGE LABEL

AZX SPORT
30 SPF
Sunscreen
1 oz. / 30 ml.
Made in Canada